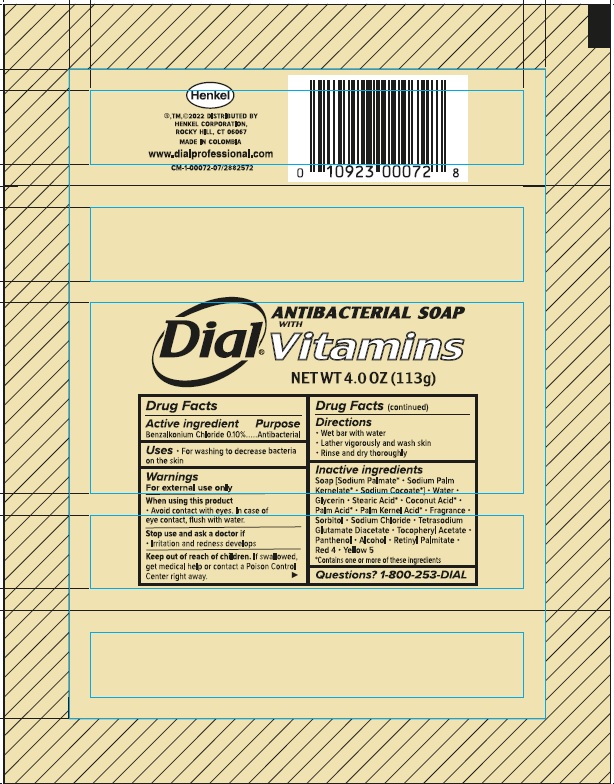 DRUG LABEL: Dial Antibacterial
NDC: 54340-020 | Form: SOAP
Manufacturer: Henkel Corporation
Category: otc | Type: HUMAN OTC DRUG LABEL
Date: 20241210

ACTIVE INGREDIENTS: BENZALKONIUM CHLORIDE 0.1 g/100 g
INACTIVE INGREDIENTS: SODIUM PALMATE; SODIUM PALM KERNELATE; SODIUM COCOATE; GLYCERIN; STEARIC ACID; COCONUT ACID; PALM ACID; PALM KERNEL ACID; SORBITOL; SODIUM CHLORIDE; ALCOHOL; VITAMIN A PALMITATE; FD&C RED NO. 4; WATER; TETRASODIUM GLUTAMATE DIACETATE; .ALPHA.-TOCOPHEROL ACETATE; PANTHENOL; FD&C YELLOW NO. 5

Dial Antibacterial Soap with Vitamins

Active ingredient

Benzalkonium Chloride 0.10%

Purpose

Antibacterial

Uses

For washing to decrease bacteria on the skin

Warnings

For external use only

When using this product

Avoid contact with eyes. In case of eye contact, flush with water,

Stop use and ask a doctor if

Irritation and redness develops

Keep out of reach of children.

If swallowed, get medical help or contact a Poison Control Center right away.

Directions

- Wet bar with water
- Lather vigorously and wash skin
- Rinse and dry thoroughly

Inactive Ingredients

Soap [Sodium Palmate*• Sodium Palm Kernelate*• Sodium Cocoate*]• Water • Glycerin • Stearic Acid*• Coconut Acid*• Palm Acid*• Palm Kernel Acid*• Fragrance • Sorbitol • Sodium Chloride • Tetrasodium Glutamate Diacetate • Tocopheryl Acetate • Panthenol • Alcohol • Retinyl Palmitate • Red 4 • Yellow 5

*Contains one or more of these ingredients

Questions?

1-800-253-DIAL

PACKAGE LABEL

Dial ANTIBACTERIAL SOAP with Vitamins

Net Wt 4.0 OZ (113 g)

Henkel

®™©2022 DISTRIBUTED BY

HENKEL CORPORATION,

ROCKY HILL, CT 06067

MADE IN COLOMBIA

www.dialprofessional.com